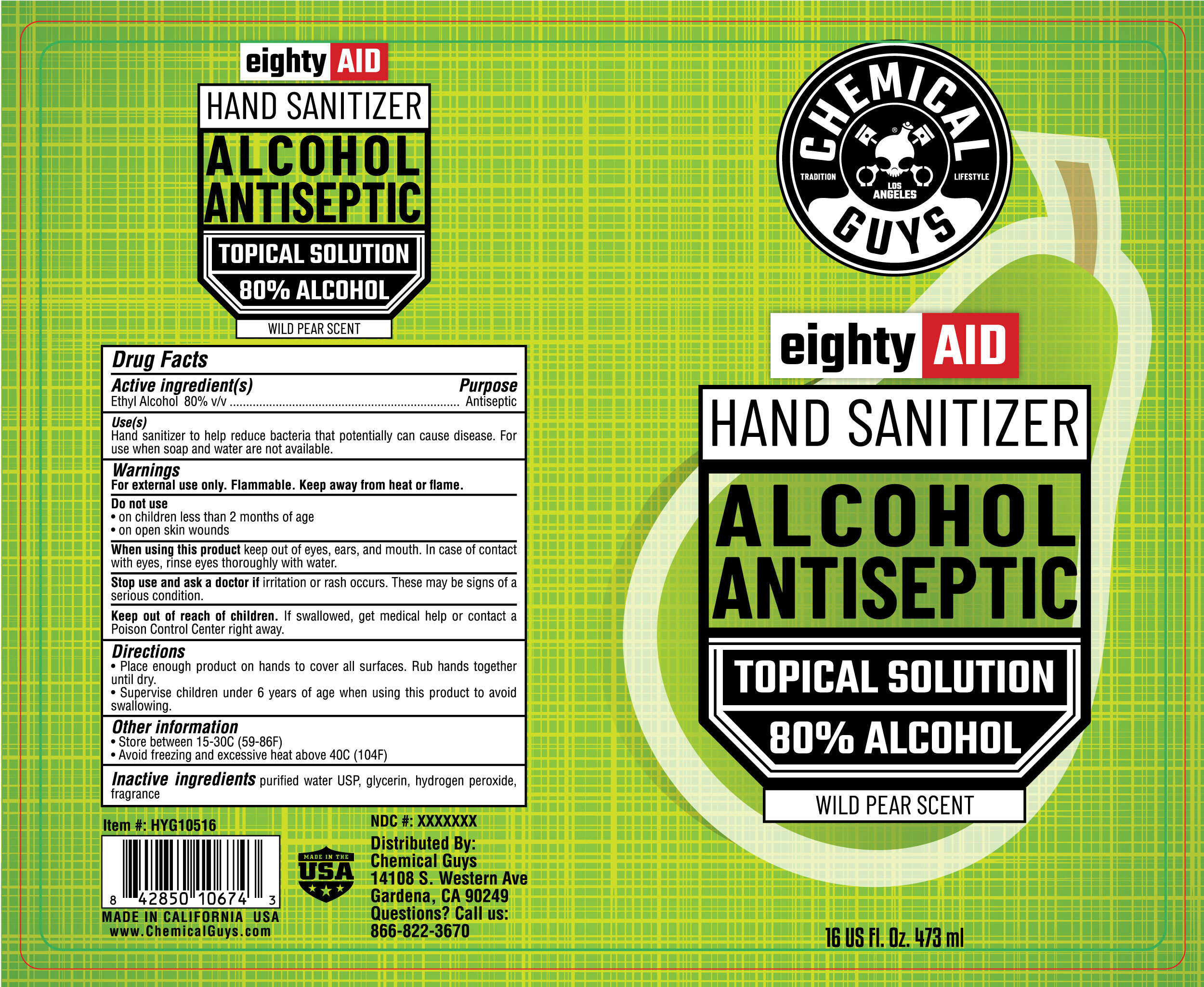 DRUG LABEL: Chemical Guys EIGHTYAID Hand Sanitizer 80% Alcohol Antiseptic Wild Pear Scent
NDC: 81112-100 | Form: GEL
Manufacturer: Chemical Guys
Category: otc | Type: HUMAN OTC DRUG LABEL
Date: 20210317

ACTIVE INGREDIENTS: ALCOHOL 80 mL/100 mL
INACTIVE INGREDIENTS: GLYCERIN; HYDROGEN PEROXIDE; PEAR; WATER

Chemical Guys EIGHTYAID Hand Sanitizer 80% Alcohol Antiseptic Wild Pear Scent

Active ingredient

Ethyl Alcohol 80%

Purpose

Antiseptic

Uses

Hand sanitizer to help reduce bacteria that potentially can cause disease. For use when soap and water are not available.

Warnings

For external use only. Flammable. Keep away from heat or flame.

Do Not Use

- On children less than 2 months of age
- On open skin wounds

When using this product avoid contact with eyes, ears, and mouth.

In case of contact with eyes, rinse eyes thoroughly with water.

Stop use or ask a doctor if

Stop use and ask a doctor if irritation or rash occurs. These may be signs of a serious condition.

Keep out of reach of children. If swallowed, get medical help or contact a Poison Control Center right away.

Directions

- Place enough product on hands to cover all surfaces. Rub hands together until dry.
- Supervise children under 6 years of age when using this product to avoid swallowing.

Other Information

- Store between 15-30^0C (59-86^0F)
- Avoid freezing and excessive heat above 40^0C (104^0F)

Inactive ingredients

water, glycerin, hydrogen peroxide, fragrance